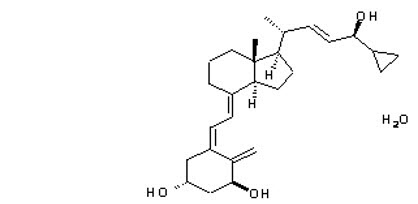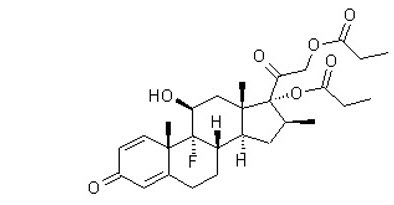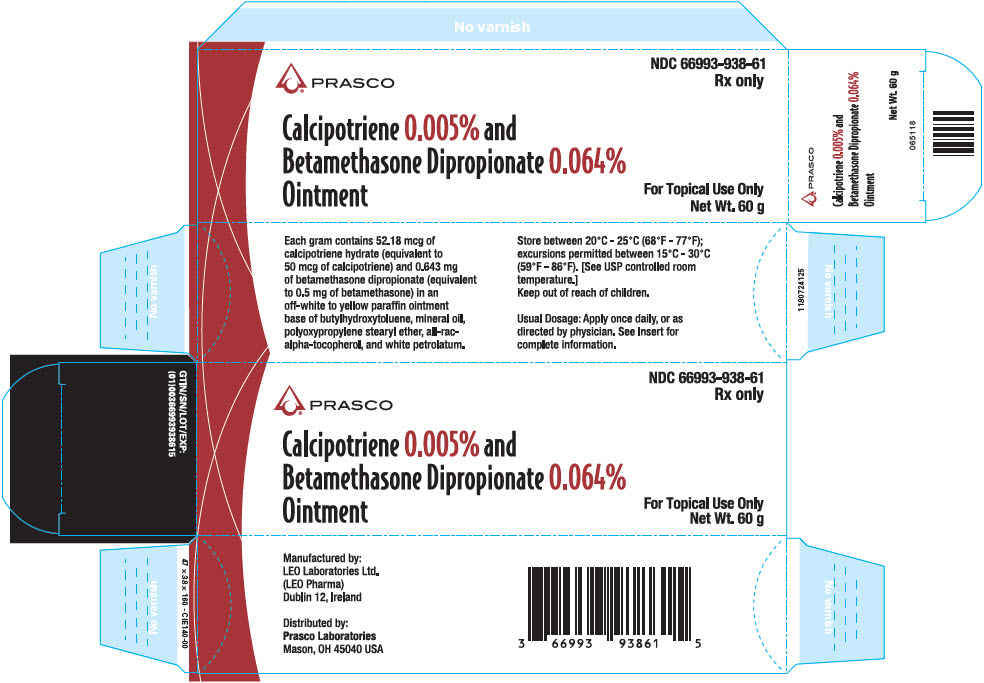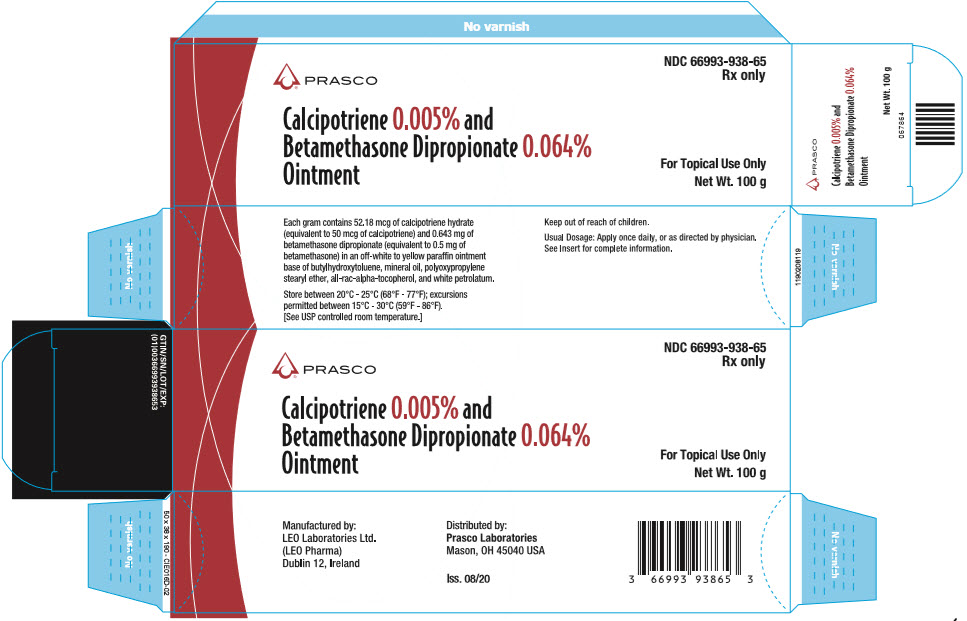 DRUG LABEL: Calcipotriene and Betamethasone Dipropionate
NDC: 66993-938 | Form: OINTMENT
Manufacturer: Prasco Laboratories
Category: prescription | Type: HUMAN PRESCRIPTION DRUG LABEL
Date: 20221212

ACTIVE INGREDIENTS: CALCIPOTRIENE MONOHYDRATE 50 ug/1 g; BETAMETHASONE DIPROPIONATE 0.5 mg/1 g
INACTIVE INGREDIENTS: .ALPHA.-TOCOPHEROL, DL-; MINERAL OIL; PETROLATUM; POLYPROPYLENE GLYCOL 11 STEARYL ETHER; BUTYLATED HYDROXYTOLUENE

HIGHLIGHTS OF PRESCRIBING INFORMATION

These highlights do not include all the information needed to use Calcipotriene and Betamethasone Dipropionate Ointment safely and effectively. See Full Prescribing Information for Calcipotriene and Betamethasone Dipropionate Ointment.
Calcipotriene and Betamethasone Dipropionate Ointment, for topical use
Initial U.S. Approval: 2006

1 INDICATIONS AND USAGE

Calcipotriene and Betamethasone Dipropionate Ointment is a vitamin D analogue and corticosteroid combination product indicated for the topical treatment of plaque psoriasis in patients 12 years of age and older. (1)

2 DOSAGE AND ADMINISTRATION

- Apply Calcipotriene and Betamethasone Dipropionate Ointment to affected area(s) once daily for up to 4 weeks. Discontinue therapy when control is achieved. (2)
- Adult patients should not use more than 100 g per week. (2)
- Patients ages 12 to 17 years should not use more than 60 g per week. (2)
- Treatment of more than 30% body surface area is not recommended. (2)
- Do not use with occlusive dressings unless directed by a physician. (2)
- Avoid use on the face, groin, or axillae, or if skin atrophy is present at the treatment site. (2)
- Not for oral, ophthalmic, or intravaginal use. (2)

3 DOSAGE FORMS AND STRENGTHS

Ointment, 0.005%/0.064% (3)

4 CONTRAINDICATIONS

None. (4)

5 WARNINGS AND PRECAUTIONS

- Hypercalcemia and hypercalciuria have been observed. If either occurs, discontinue treatment until parameters of calcium metabolism normalize. (5.1)
- Calcipotriene and Betamethasone Dipropionate Ointment can produce reversible hypothalamic-pituitary-adrenal (HPA) axis suppression with the potential for glucocorticosteroid insufficiency during and after withdrawal of treatment. Risk factors include the use of high-potency topical corticosteroid, use over a large surface area or to areas under occlusion, prolonged use, concomitant use of more than one corticosteroid-containing product, altered skin barrier, liver failure, and use in pediatric patients. Modify use should HPA axis suppression develop. (5.2, 8.4)
- Calcipotriene and Betamethasone Dipropionate Ointment may increase the risk of cataract and glaucoma. If visual symptoms occur, consider referral to an ophthalmologist. (5.3)

6 ADVERSE REACTIONS

The most common adverse reactions (≥1%) are pruritus and scaly rash. (6.1)

To report SUSPECTED ADVERSE REACTIONS, contact LEO Pharma Inc. at 1-877-494-4536 or FDA at 1-800-FDA-1088 or www.fda.gov/medwatch.

FULL PRESCRIBING INFORMATION

1 INDICATIONS AND USAGE

Calcipotriene and Betamethasone Dipropionate Ointment is indicated for the topical treatment of plaque psoriasis in patients 12 years of age and older.

2 DOSAGE AND ADMINISTRATION

Apply an adequate layer of Calcipotriene and Betamethasone Dipropionate Ointment to the affected area(s) once daily for up to 4 weeks. Calcipotriene and Betamethasone Dipropionate Ointment should be rubbed in gently and completely. Patients should wash their hands after applying Calcipotriene and Betamethasone Dipropionate Ointment. Therapy should be discontinued when control is achieved.

Patients 18 years and older should not use more than 100 g per week and patients 12 to 17 years should not use more than 60 g per week. Treatment of more than 30% body surface area is not recommended.

Calcipotriene and Betamethasone Dipropionate Ointment should not be used with occlusive dressings unless directed by a physician. Avoid use on the face, groin, or axillae, or if skin atrophy is present at the treatment site. Calcipotriene and Betamethasone Dipropionate Ointment is not for oral, ophthalmic, or intravaginal use.

3 DOSAGE FORMS AND STRENGTHS

Ointment, 0.005%/0.064%

Each gram of Calcipotriene and Betamethasone Dipropionate Ointment contains 52.18 mcg of calcipotriene hydrate (equivalent to 50 mcg of calcipotriene) and 0.643 mg of betamethasone dipropionate (equivalent to 0.5 mg of betamethasone) in off-white to yellow paraffin ointment base.

4 CONTRAINDICATIONS

None.

5 WARNINGS AND PRECAUTIONS

5.1 Hypercalcemia and Hypercalciuria

Hypercalcemia and hypercalciuria have been observed with use of Calcipotriene and Betamethasone Dipropionate Ointment. If hypercalcemia or hypercalciuria develops, treatment should be discontinued until parameters of calcium metabolism have normalized. In the trials that included assessment of the effects of Calcipotriene and Betamethasone Dipropionate Ointment on calcium metabolism, such testing was done after 4 weeks of treatment. The effects of Calcipotriene and Betamethasone Dipropionate Ointment on calcium metabolism following treatment durations of longer than 4 weeks have not been evaluated [see Clinical Pharmacology (12.2)].

5.2 Effects on Endocrine System

Calcipotriene and Betamethasone Dipropionate Ointment can cause reversible hypothalamic-pituitary-adrenal (HPA) axis suppression with the potential for clinical glucocorticosteroid insufficiency. This may occur during treatment or upon withdrawal of treatment. Factors that predispose a patient to HPA axis suppression include the use of high-potency corticosteroids, large treatment surface areas, prolonged use, concomitant use of more than one corticosteroid-containing product, use of occlusive dressings, altered skin barrier, liver failure, and young age. Evaluation for HPA axis suppression may be done by using the cosyntropin stimulation test [see Clinical Pharmacology (12.2)].

In a trial evaluating the effects of Calcipotriene and Betamethasone Dipropionate Topical Suspension and Calcipotriene and Betamethasone Dipropionate Ointment on the HPA axis, 32 adult subjects were treated with Calcipotriene and Betamethasone Dipropionate Topical Suspension on the scalp and Calcipotriene and Betamethasone Dipropionate Ointment on the body. Adrenal suppression was identified in 5 of 32 subjects (15.6%) after 4 weeks of treatment [see Clinical Pharmacology (12.2)]. The effects of Calcipotriene and Betamethasone Dipropionate Ointment on the HPA axis following treatment durations of longer than 4 weeks have not been adequately studied.

If HPA axis suppression is documented, gradually withdraw the drug, reduce the frequency of application, or substitute with a less potent corticosteroid.

Cushing's syndrome and hyperglycemia may also occur due to the systemic effects of topical corticosteroids. These complications are rare and generally occur after prolonged exposure to excessively large doses, especially of high-potency topical corticosteroids.

Pediatric patients may be more susceptible to systemic toxicity due to their higher skin surface to body mass ratios [see Use in Specific Populations (8.4), Clinical Pharmacology (12.2)].

Use of more than one corticosteroid-containing product at the same time may increase the total systemic corticosteroid exposure.

5.3 Ophthalmic Adverse Reactions

Use of topical corticosteroids, including Calcipotriene and Betamethasone Dipropionate Ointment, may increase the risks of glaucoma and posterior subcapsular cataract. Glaucoma and cataracts have been reported in postmarketing experience with the use of topical corticosteroid products, including topical clobetasol products.

Avoid contact of Calcipotriene and Betamethasone Dipropionate Ointment with eyes. Advise patients to report any visual symptoms and consider referral to an ophthalmologist for evaluation.

5.4 Allergic Contact Dermatitis with Topical Corticosteroids

Allergic contact dermatitis to any component of topical corticosteroids is usually diagnosed by a failure to heal rather than a clinical exacerbation. Clinical diagnosis of allergic contact dermatitis can be confirmed by patch testing.

5.5 Allergic Contact Dermatitis with Topical Calcipotriene

Allergic contact dermatitis has been observed with use of topical calcipotriene. Clinical diagnosis of allergic contact dermatitis can be confirmed by patch testing.

5.6 Skin Irritation

If irritation develops, treatment with Calcipotriene and Betamethasone Dipropionate Ointment should be discontinued and appropriate therapy instituted.

5.7 Risk of Ultraviolet Light Exposure

Patients who apply Calcipotriene and Betamethasone Dipropionate Ointment to exposed skin should avoid excessive exposure to either natural or artificial sunlight, including tanning booths, sun lamps, etc. Physicians may wish to limit or avoid use of phototherapy in patients who use Calcipotriene and Betamethasone Dipropionate Ointment.

6 ADVERSE REACTIONS

Because clinical trials are conducted under widely varying conditions, adverse reaction rates observed in the clinical trials of a drug cannot be directly compared to rates in the clinical trials of another drug and may not reflect the rates observed in practice.

6.1 Clinical Trials Experience

Clinical Trials Conducted in Subjects 18 years and older with Plaque Psoriasis

The data described below reflect exposure to Calcipotriene and Betamethasone Dipropionate Ointment in 2448 subjects with plaque psoriasis, including 1992 exposed for 4 weeks, and 289 exposed for 8 weeks.

Calcipotriene and Betamethasone Dipropionate Ointment was studied primarily in placebo- and active-controlled trials (N = 1176, and N = 1272, respectively). The population was 15-97 years old, 61% males and 39% females, mostly white (97%) and had a baseline disease severity ranging from mild to very severe. Most subjects received once daily application, and the median weekly dose was 24.5 g.

The percentage of subjects reporting at least one adverse event was 27.1% in the Calcipotriene and Betamethasone Dipropionate Ointment group, 33.0% in the calcipotriene group, 28.3% in the betamethasone group, and 33.4% in the vehicle group.

Table 1 Adverse Events Reported by ≥1% of Subjects by Preferred Term
 | Calcipotriene and Betamethasone Dipropionate Ointment | Calcipotriene | Betamethasone dipropionate | Vehicle
 | N = 2448 | N = 3197 | N = 1164 | N = 470
Any Adverse Event | 663 (27.1) | 1055 (33.0) | 329 (28.3) | 157 (33.4)
Preferred Term | # of subjects (%)
Pruritus | 75 (3.1) | 183 (5.7) | 38 (3.3) | 43 (9.1)
Headache | 69 (2.8) | 75 (2.3) | 44 (3.8) | 12 (2.6)
Nasopharyngitis | 56 (2.3) | 77 (2.4) | 34 (2.9) | 9 (1.9)
Psoriasis | 30 (1.2) | 47 (1.5) | 14 (1.2) | 5 (1.1)
Rash scaly | 30 (1.2) | 40 (1.3) | 0 (0.0) | 1 (0.2)
Influenza | 23 (0.9) | 34 (1.1) | 14 (1.2) | 6 (1.3)
Upper respiratory tract infection | 20 (0.8) | 19 (0.6) | 12 (1.0) | 3 (0.6)
Erythema | 15 (0.6) | 54 (1.7) | 3 (0.3) | 5 (1.1)
Application site pruritus | 13 (0.5) | 24 (0.8) | 10 (0.9) | 6 (1.3)
Skin irritation | 11 (0.4) | 60 (1.9) | 8 (0.7) | 5 (1.1)
Pain | 7 (0.3) | 12 (0.4) | 3 (0.3) | 5 (1.1)
Burning sensation | 6 (0.2) | 30 (0.9) | 3 (0.3) | 6 (1.3)

A lesional/perilesional adverse event was generally defined as an adverse event located ≤ 2 cm from the lesional border.

Table 2 Lesional/Perilesional Adverse Events Reported by ≥1% of Subjects
 | Calcipotriene and Betamethasone Dipropionate Ointment | Calcipotriene | Betamethasone dipropionate | Vehicle
 | N = 2448 | N = 3197 | N = 1164 | N = 470
Any Adverse Event | 213 (8.7) | 419 (13.1) | 85 (7.3) | 76 (16.2)
Preferred Term | # of subjects (%)
Pruritus | 69 (2.8) | 170 (5.3) | 31 (2.7) | 41 (8.7)
Rash scaly | 29 (1.2) | 38 (1.2) | 0 (0.0) | 0 (0.0)
Application site pruritus | 12 (0.5) | 24 (0.8) | 10 (0.9) | 6 (1.3)
Erythema | 9 (0.4) | 36 (1.1) | 2 (0.2) | 4 (0.9)
Skin irritation | 9 (0.4) | 51 (1.6) | 8 (0.7) | 5 (1.1)
Burning sensation | 6 (0.2) | 25 (0.8) | 3 (0.3) | 5 (1.1)

For subjects who reported lesional/perilesional adverse events, the median time to onset was 7 days for Calcipotriene and Betamethasone Dipropionate Ointment, 7 days for calcipotriene, 5 days for betamethasone dipropionate, and 3 days for vehicle.

Other less common reactions (less than 1% but more than 0.1%) were, in decreasing order of incidence, folliculitis, rash papular, rash pustular, and skin hypopigmentation. Skin atrophy, telangiectasia and skin hyperpigmentation were reported infrequently (0.1%).

In a separate trial, subjects (N = 207) with at least moderate disease severity were given Calcipotriene and Betamethasone Dipropionate Ointment intermittently on an "as needed" basis for up to 52 weeks. The median use was 15.4 g per week. The effects of Calcipotriene and Betamethasone Dipropionate Ointment on calcium metabolism were not studied and the effects on the HPA axis were not adequately studied. The following adverse reactions were reported by 1% or more of the subjects: pruritus (7.2%), psoriasis (3.4%), skin atrophy (1.9%), folliculitis (1.4%), burning sensation (1.4%), skin depigmentation (1.4%), ecchymosis (1.0%), erythema (1.0%) and hand dermatitis (1.0%). One case of serious flare-up of psoriasis was reported.

6.2 Postmarketing Experience

The following adverse reactions associated with the use of Calcipotriene and Betamethasone Dipropionate Ointment have been identified post-approval: pustular psoriasis and rebound effect.

Because these reactions are reported voluntarily from a population of uncertain size, it is not always possible to reliably estimate their frequency or establish a causal relationship to drug exposure.

Postmarketing reports for local adverse reactions to topical corticosteroids may also include: striae, dryness, acneiform eruptions, perioral dermatitis, secondary infection and miliaria.

8 USE IN SPECIFIC POPULATIONS

8.1 Pregnancy

Risk Summary

Calcipotriene and Betamethasone Dipropionate Ointment contains calcipotriene and betamethasone dipropionate. The limited data with Calcipotriene and Betamethasone Dipropionate Ointment and calcipotriene use in pregnant women are not sufficient to evaluate a Calcipotriene and Betamethasone Dipropionate Ointment-associated or calcipotriene-associated risk for major birth defects, miscarriages, or adverse maternal or fetal outcomes.

Observational studies suggest an increased risk of having low birthweight infants with the maternal use of potent or very potent topical corticosteroids (see Data). Advise pregnant women that Calcipotriene and Betamethasone Dipropionate Ointment may increase the potential risk of having a low birth weight infant and to use Calcipotriene and Betamethasone Dipropionate Ointment on the smallest area of skin and for the shortest duration possible.

In animal reproduction studies, oral administration of calcipotriene to pregnant rats during the period of organogenesis resulted in an increased incidence of minor skeletal abnormalities, including enlarged fontanelles and extra ribs (see Data). Oral administration of calcipotriene to pregnant rabbits during the period of organogenesis had no apparent effects on embryo-fetal development. Subcutaneous administration of betamethasone dipropionate to pregnant rats and rabbits during the period of organogenesis resulted in fetal toxicity, including fetal deaths, reduced fetal weight, and fetal malformations (cleft palate and crooked or short tail) (see Data). The available data do not allow the calculation of relevant comparisons between the systemic exposures of calcipotriene and betamethasone diproprionate observed in animal studies to the systemic exposures that would be expected in humans after topical use of Calcipotriene and Betamethasone Dipropionate Ointment.

The estimated background risk of major birth defects and miscarriage of the indicated population is unknown. In the U.S. general population, the estimated background risk of major birth defects and miscarriage in clinically recognized pregnancies is 2% to 4% and 15% to 20%, respectively.

Data

Human Data

Available observational studies in pregnant women did not identify a drug-associated risk of major birth defects, preterm delivery, or fetal mortality with the use of topical corticosteroids of any potency. However, when the dispensed amount of potent or very potent topical corticosteroids exceeded 300 g during the entire pregnancy, maternal use was associated with an increased risk of low birth weight in infants.

Animal Data

Embryo-fetal development studies with calcipotriene were performed by the oral route in rats and rabbits. Pregnant rats received dosages of 0, 6, 18, or 54 mcg/kg/day (0, 36, 108, and 324 mcg/m^2/day, respectively) on days 6-15 of gestation (the period of organogenesis). There were no apparent effects on maternal survival, behavior, or body weight gain, no effects on litter parameters, and no effects on the incidence of major malformations in fetuses. Fetuses from dams dosed at 54 mcg/kg/day exhibited a significantly increased incidence of minor skeletal abnormalities, including enlarged fontanelles and extra ribs.

Pregnant rabbits were dosed daily with calcipotriene at exposures of 0, 4, 12, or 36 mcg/kg/day (0, 48, 144, and 432 mcg/m^2/day, respectively) on days 6-18 of gestation (the period of organogenesis). Mean maternal body weight gain was reduced in animals dosed at 12 or 36 mcg/kg/day. The incidence of fetal deaths was increased in the group dosed at 36 mcg/kg/day; reduced fetal weight was also observed in this group. The incidence of major malformations among fetuses was not affected. An increase in the incidence of minor skeletal abnormalities, including incomplete ossification of sternebrae, pubic bones, and forelimb phalanges, was observed in the group dosed at 36 mcg/kg/day.

Embryo-fetal development studies with betamethasone dipropionate were performed via subcutaneous injection in mice and rabbits. Pregnant mice were administered doses of 0, 156, 625, or 2500 mcg/kg/day (0, 468, 1875, and 7500 mcg/m^2/day, respectively) on days 7 through 13 of gestation (the period of organogenesis). Betamethasone dipropionate induced fetal toxicity, including fetal deaths, reduced fetal weight, malformations (increased incidence of the cleft palate and crooked or short tail), and minor skeletal abnormalities (delayed ossification of vertebra and sternebrae). Fetal toxicity was observed at the lowest exposure that was evaluated (156 mcg/kg/day).

Pregnant rabbits were injected subcutaneously at dosages of 0, 0.625, 2.5, and 10 mcg/kg/day (0, 7.5, 30, and 120 mcg/m^2/day, respectively) on days 6 through 18 of gestation (the period of organogenesis). Betamethasone dipropionate induced fetal toxicity, including fetal deaths, reduced fetal weight, external malformations (including malformed ears, cleft palate, umbilical hernia, kinked tail, club foot, and club hand), and skeletal malformations (including absence of phalanges of the first digit and cranial dysplasia) at dosages of 2.5 mcg/kg/day and above.

Calcipotriene was evaluated for effects on peri- and post-natal development when orally administered to pregnant rats at dosages of 0, 6, 18 or 54 mcg/kg/day (0, 36, 108, and 324 mcg/m^2/day, respectively) from gestation day 15 through day 20 postpartum. No remarkable effects were observed on any parameter, including survival, behavior, body weight, litter parameters, or the ability to nurse or rear pups.

Betamethasone dipropionate was evaluated for effects on peri- and post-natal development when orally administered to pregnant rats at dosages of 0, 100, 300, and 1000 mcg/kg/day (0, 600, 1800, and 6000 mcg/m^2/day, respectively) from gestation day 6 through day 20 postpartum. Mean maternal body weight was significantly reduced on gestation day 20 in animals dosed at 300 and 1000 mcg/kg/day. The mean duration of gestation was slightly, but statistically significantly, increased at 100, 300, and 1000 mcg/kg/day. The mean percentage of pups that survived to day 4 was reduced in relation to dosage. On lactation day 5, the percentage of pups with a reflex to right themselves when placed on their back was significantly reduced at 1000 mcg/ kg/day. No effects on the ability of pups to learn were observed, and the ability of the offspring of treated rats to reproduce was not affected.

8.2 Lactation

Risk Summary

There is no information regarding the presence of topically administered calcipotriene and betamethasone dipropionate in human milk, the effects on the breastfed infant, or the effects on milk production. It is not known whether topically administered calcipotriene or corticosteroids could result in sufficient systemic absorption to produce detectable quantities in human milk. The developmental and health benefits of breastfeeding should be considered along with the mother's clinical need for Calcipotriene and Betamethasone Dipropionate Ointment and any potential adverse effects on the breastfed child from Calcipotriene and Betamethasone Dipropionate Ointment or from the underlying maternal condition.

Clinical Considerations

To minimize potential exposure to the breastfed infant via breast milk, use Calcipotriene and Betamethasone Dipropionate Ointment on the smallest area of skin and for the shortest duration possible while breastfeeding. Advise breastfeeding women not to apply Calcipotriene and Betamethasone Dipropionate Ointment directly to the nipple and areola to avoid direct infant exposure [see Use in Specific Populations (8.4)].

8.4 Pediatric Use

Safety and effectiveness of the use of Calcipotriene and Betamethasone Dipropionate Ointment in pediatric patients under the age of 12 years have not been established.

The safety and effectiveness of Calcipotriene and Betamethasone Dipropionate Ointment for the treatment of plaque psoriasis have been established in the age group 12 to 17 years. In a prospective, uncontrolled trial, 33 pediatric subjects ages 12-17 years with plaque psoriasis on the body were treated with Calcipotriene and Betamethasone Dipropionate Ointment for 4 weeks up to a maximum of 55.8 g per week. Subjects were assessed for HPA axis suppression and effects on calcium metabolism. No adverse effects on adrenal suppression were observed. No hypercalcemia was observed but one subject had a possible treatment-related increase in urinary calcium [see Clinical Pharmacology (12.2)].

Because of a higher ratio of skin surface area to body mass, pediatric patients are at a greater risk than adults of systemic toxicity when treated with topical drugs. They are, therefore, also at greater risk of HPA axis suppression and adrenal insufficiency upon the use of topical corticosteroids [see Warnings and Precautions (5.2)].

Rare systemic toxicities such as Cushing's syndrome, linear growth retardation, delayed weight gain, and intracranial hypertension have been reported in pediatric patients, especially those with prolonged exposure to large doses of high potency topical corticosteroids.

Local adverse reactions including striae have also been reported with use of topical corticosteroids in pediatric patients.

8.5 Geriatric Use

Of the total number of subjects in the clinical studies of Calcipotriene and Betamethasone Dipropionate Ointment, approximately 14% were 65 years and older and approximately 3% were 75 years and over.

No overall differences in safety or effectiveness of Calcipotriene and Betamethasone Dipropionate Ointment were observed between these subjects and younger subjects. All other reported clinical experience has not identified any differences in response between elderly and younger patients. However, greater sensitivity of some older individuals cannot be ruled out.

10 OVERDOSAGE

Topically applied Calcipotriene and Betamethasone Dipropionate Ointment can be absorbed in sufficient amounts to produce systemic effects [see Warnings and Precautions (5.1, 5.2)].

11 DESCRIPTION

Calcipotriene and Betamethasone Dipropionate Ointment, 0.005%/0.064% contains calcipotriene hydrate and betamethasone dipropionate. It is intended for topical use only.

Calcipotriene hydrate is a synthetic vitamin D3 analogue.

Chemically, calcipotriene hydrate is (5Z,7E,22E,24S)-24-cyclopropyl-9,10-secochola-5,7,10(19),22-tetraene-1(alpha),3(beta),24-triol,hydrate, with the empirical formula C27H40O3,H2O, a molecular weight of 430.6, and the following structural formula:

Calcipotriene hydrate is a white to almost white crystalline compound.

Betamethasone dipropionate is a synthetic corticosteroid.

Betamethasone dipropionate has the chemical name 9-fluoro-11(beta), 17,21-trihydroxy-16(beta)-methylpregna-1,4-diene-3,20-dione17,21-dipropionate, with the empirical formula C28H37FO7, a molecular weight of 504.6, and the following structural formula:

Betamethasone dipropionate is a white to almost white odorless powder.

Each gram of Calcipotriene and Betamethasone Dipropionate Ointment contains 52.18 mcg of calcipotriene hydrate (equivalent to 50 mcg of calcipotriene) and 0.643 mg of betamethasone dipropionate (equivalent to 0.5 mg of betamethasone) in an off-white to yellow paraffin ointment base of butylhydroxytoluene, mineral oil, polyoxypropylene stearyl ether, all-rac-alpha-tocopherol, and white petrolatum.

12 CLINICAL PHARMACOLOGY

12.1 Mechanism of Action

Calcipotriene and Betamethasone Dipropionate Ointment combines the pharmacological effects of calcipotriene hydrate as a synthetic vitamin D3 analogue and betamethasone dipropionate as a synthetic corticosteroid. However, while their pharmacologic and clinical effects are known, the exact mechanisms of their actions in plaque psoriasis are unknown.

12.2 Pharmacodynamics

Vasoconstriction:

In a vasoconstrictor trial in healthy subjects, the skin blanching response of Calcipotriene and Betamethasone Dipropionate Ointment was consistent with that of a potent corticosteroid when compared with other topical corticosteroids. However, similar blanching scores do not necessarily imply therapeutic equivalence.

Hypothalamic-Pituitary-Adrenal (HPA) Axis Suppression:

HPA axis suppression was evaluated in four trials (Trial A, B, C and D) following the application of Calcipotriene and Betamethasone Dipropionate Ointment.

In Trial A, Calcipotriene and Betamethasone Dipropionate Ointment was applied once daily for 4 weeks to adult subjects (N = 12) with plaque psoriasis to study its effects on the hypothalamic-pituitary-adrenal (HPA) axis. Of eleven subjects tested, none demonstrated adrenal suppression as indicated by a 30-minute post-stimulation cortisol level ≤ 18 mcg/dL.

In Trial B, Calcipotriene and Betamethasone Dipropionate Ointment was evaluated in adult subjects with plaque psoriasis (N = 19). One subject demonstrated adrenal suppression.

In Trial C, HPA axis suppression was evaluated in adult subjects (N=32) with extensive plaque psoriasis involving at least 30% of the scalp and, in total, 15-30% of the body surface area. Treatment consisted of once daily application of Taclonex Scalp® Topical Suspension on the scalp in combination with Calcipotriene and Betamethasone Dipropionate Ointment on the body. Adrenal suppression as indicated by a 30-minutes post-stimulation cortisol level < 18 mcg/dL was observed in 5 of 32 subjects (15.6%) after 4 weeks of treatment as per the recommended duration of use [see Dosage and Administration (2)].

In Trial D, HPA axis suppression was evaluated in subjects 12 to 17 years (N=32) with plaque psoriasis of the body involving 5-30% of the body surface area. Treatment consisted of once daily application of Calcipotriene and Betamethasone Dipropionate Ointment to the affected areas for up to 4 weeks. Mean weekly dose was 29.6 g with a range of 8.1-55.8 g/week. Adrenal suppression as indicated by a 30-minute post-stimulation cortisol level ≤18 mcg/dL was observed in none of 32 evaluable subjects after 4 weeks of treatment [see Use in Specific Populations (8.4)].

Effects on Calcium Metabolism

In Trial C described above, the effects of once daily application of Calcipotriene and Betamethasone Dipropionate Ointment on the body in combination with Taclonex Scalp® Topical Suspension on the scalp on calcium metabolism were also examined. Elevated urinary calcium levels outside the normal range were observed in 1 of 35 subjects (2.9%) after 4 weeks of treatment.

In Trial D described above, calcium metabolism was evaluated in a total of 33 subjects aged 12 to 17 years with plaque psoriasis involving 5-30% of the body surface area who underwent once daily application of Calcipotriene and Betamethasone Dipropionate Ointment for up to 4 weeks. No cases of hypercalcemia and no clinically relevant changes in urinary calcium were reported. However, one subject had a normal urinary calcium:creatinine ratio at baseline (3.75 mmol/g), which increased above the normal range at week 4 (16 mmol/g). There were no relevant changes in albumin-corrected serum calcium or other markers of calcium metabolism for this subject. The clinical significance of this finding is unknown.

12.3 Pharmacokinetics

Absorption

In Trial C described above, the systemic effect of Calcipotriene and Betamethasone Dipropionate Ointment in extensive plaque psoriasis was investigated. In this trial, the serum levels of calcipotriene and betamethasone dipropionate and their major metabolites were measured after 4 weeks (maximum recommended duration of treatment) and also after 8 weeks of once daily application of Calcipotriene and Betamethasone Dipropionate Ointment on the body in combination with Taclonex Scalp® Topical Suspension on the scalp. Both calcipotriene and betamethasone dipropionate were below the lower limit of quantification in all serum samples of the 34 subjects evaluated. However, one major metabolite of calcipotriene (MC1080) was quantifiable in 10 of 34 (29.4%) subjects at week 4 and in five of 12 (41.7%) subjects at week 8. The major metabolite of betamethasone dipropionate, betamethasone 17-propionate (B17P) was also quantifiable in 19 of 34 (55.9%) subjects at week 4 and seven of 12 (58.3%) subjects at week 8. The serum concentrations for MC1080 ranged from 20-75 pg/mL. The clinical significance of this finding is unknown.

Metabolism

Calcipotriene:

Calcipotriene metabolism following systemic uptake is rapid and occurs in the liver. The primary metabolites of calcipotriene are less potent than the parent compound.

Calcipotriene is metabolized to MC1046 (the alpha,beta-unsaturated ketone analogue of calcipotriene), which is metabolized further to MC1080 (a saturated ketone analogue). MC1080 is the major metabolite in plasma. MC1080 is slowly metabolized to calcitroic acid.

Betamethasone dipropionate:

Betamethasone dipropionate is metabolized to betamethasone 17-propionate and betamethasone, including the 6beta-hydroxy derivatives of those compounds by hydrolysis. Betamethasone 17-propionate (B17P) is the primary metabolite.

13 NONCLINICAL TOXICOLOGY

13.1 Carcinogenesis, Mutagenesis, Impairment of Fertility

When calcipotriene was applied topically to mice for up to 24 months at dosages of 3, 10 and 30 mcg/kg/day (9, 30 and 90 mcg/m^2/day, respectively), no significant changes in tumor incidence were observed when compared to control.

A 104-week oral carcinogenicity study was conducted with calcipotriene in male and female rats at doses of 1, 5 and 15 mcg/kg/day (6, 30, and 90 mcg/m^2/day, respectively). Beginning week 71, the dosage for high-dose animals of both genders was reduced to 10 mcg/kg/day (60 mcg/m^2/day). A treatment-related increase in benign C-cell adenomas was observed in the thyroid of females that received 15 mcg/kg/day. A treatment-related increase in benign pheochromocytomas was observed in the adrenal glands of males that received 15 mcg/kg/day. No other statistically significant differences in tumor incidence were observed when compared to control. The relevance of these findings to patients is unknown.

When betamethasone dipropionate was applied topically to CD-1 mice for up to 24 months at dosages approximating 1.3, 4.2 and 8.5 mcg/kg/day in females, and 1.3, 4.2, and 12.9 mcg/kg/day in males (up to 26 mcg/m^2/day and 39 mcg/m^2/day, in females and males, respectively), no significant changes in tumor incidence were observed when compared to control.

When betamethasone dipropionate was administered via oral gavage to male and female Sprague Dawley rats for up to 24 months at dosages of 20, 60, and 200 mcg/kg/day (120, 360, and 1200 mcg/m^2/day, respectively), no significant changes in tumor incidence were observed when compared to control.

Calcipotriene did not elicit any genotoxic effects in the Ames mutagenicity assay, the mouse lymphoma TK locus assay, the human lymphocyte chromosome aberration test, or the mouse micronucleus test. Betamethasone dipropionate did not elicit any genotoxic effects in the Ames mutagenicity assay, the mouse lymphoma TK locus assay, or in the rat micronucleus test.

Studies in rats with oral doses of up to 54 mcg/kg/day (324 mcg/m^2/day) of calcipotriene indicated no impairment of fertility or general reproductive performance. Studies in male rats at oral doses of up to 200 mcg/kg/day (1200 mcg/m^2/day), and in female rats at oral doses of up to 1000 mcg/kg/day (6000 mcg/m^2/day), of betamethasone dipropionate indicated no impairment of fertility.

14 CLINICAL STUDIES

Clinical Trials Conducted in Subjects 18 years and older with Plaque Psoriasis

In an international, multi-center, double-blind, vehicle- and active-controlled, parallel-group trial, 1603 subjects with mild to very severe plaque psoriasis on trunk and limbs were treated once daily for 4 weeks. Subjects were randomized to one of four treatment arms: Calcipotriene and Betamethasone Dipropionate Ointment, calcipotriene hydrate 50 mcg/g in the same vehicle, betamethasone dipropionate 0.64 mg/g in the same vehicle, and vehicle alone. The mean age of the subjects was 48.4 years and 60.5% were male. Most subjects had disease of moderate severity at baseline.

Efficacy was assessed as the proportion of subjects with absent or very mild disease according to the Investigator's Global Assessment of Disease Severity at end of treatment (4 weeks). "Absent" disease was defined as no evidence of redness, thickness, or scaling. "Very mild disease" was defined as controlled disease, but not entirely cleared: lesions with some discoloration with absolutely minimal thickness, i.e. the edges to the lesion(s) could just be felt. Table 3 contains the response rates for this trial.

Table 3 Percentage of Subjects with Absent or Very Mild Disease According to the Investigator's Global Assessment of Disease Severity at End of Treatment (4 weeks) [Subjects with mild disease at baseline were required to have "Absent" disease to be considered a success.]
 | Calcipotriene and Betamethasone Dipropionate Ointment | Calcipotriene | Betamethasone dipropionate | Vehicle
 | N = 490 | N = 480 | N = 476 | N = 157
Absent or very mild disease | 48.0% | 16.5% | 26.3% | 7.6%

In addition to the pivotal trial (N = 490), four randomized, double-blind, vehicle- or active-controlled, parallel-group trials were conducted and provided supportive evidence of efficacy. These trials included a total of 1058 subjects treated with Calcipotriene and Betamethasone Dipropionate Ointment once daily for up to 4 weeks.

Clinical Trial Conducted in Subjects 12 to 17 years with Plaque Psoriasis

A prospective, uncontrolled trial (N=33) was conducted in pediatric subjects ages 12 to 17 years with plaque psoriasis involving 5-30% of the body surface area. Approximately 91% of subjects had moderate disease at baseline. Subjects were treated once daily for up to 4 weeks with Calcipotriene and Betamethasone Dipropionate Ointment. All subjects were evaluated for safety including calcium metabolism (N=33) and 32 subjects were evaluated for HPA axis suppression [see Clinical Pharmacology (12.2)].

16 HOW SUPPLIED/STORAGE AND HANDLING

16.1 How Supplied

Calcipotriene and Betamethasone Dipropionate Ointment is off-white to yellow in color, available in collapsible tubes of:

60 gram (NDC 66993-938-61)
100 gram (NDC 66993-938-65)

16.2 Storage

Store Calcipotriene and Betamethasone Dipropionate Ointment between 20°C - 25°C (68°F - 77°F); excursions permitted between 15°C - 30°C (59°F - 86°F). [See USP controlled room temperature.]

16.3 Handling

Keep out of reach of children.

17 PATIENT COUNSELING INFORMATION

See FDA-approved patient labeling (Patient Information).

Inform patients of the following:

- Instruct adult patients (18 years and older) not to use more than 100 g per week.
- Instruct pediatric patients (12 to 17 years) not to use more than 60 g per week.
- Discontinue therapy when control is achieved unless directed otherwise by the physician.
- Avoid use of Calcipotriene and Betamethasone Dipropionate Ointment on the face, underarms, groin or eyes. If this medicine gets on face or in eyes, wash area right away.
- Do not occlude the treatment area with a bandage or other covering unless directed by the physician.
- Note that local reactions and skin atrophy are more likely to occur with occlusive use, prolonged use or use of higher potency corticosteroids.
- Wash hands after application.
- Advise patients to report any visual symptoms to their healthcare providers.
- Advise a woman to use Calcipotriene and Betamethasone Dipropionate Ointment on the smallest area of skin and for the shortest duration possible while pregnant or breastfeeding. Advise breastfeeding women not to apply Calcipotriene and Betamethasone Dipropionate Ointment directly to the nipple and areola to avoid direct infant exposure.
- Instruct patients not to use other products containing calcipotriene or a corticosteroid should not be used with Calcipotriene and Betamethasone Dipropionate Ointment without first talking to the physician.
- Instruct patients who use Calcipotriene and Betamethasone Dipropionate Ointment to avoid excessive exposure to either natural or artificial sunlight (including tanning booths, sun lamps, etc.).

Manufactured by:
LEO Laboratories Ltd. (LEO Pharma)
Dublin 12, Ireland

Distributed by:
Prasco Laboratories
Mason, OH 45040 USA

PATIENT INFORMATION Calcipotriene and Betamethasone Dipropionate Ointment, 0.005%/0.064%

Read the Patient Information that comes with Calcipotriene and Betamethasone Dipropionate Ointment before you start using it and each time you refill your prescription. There may be new information. This leaflet does not take the place of talking with your doctor about your condition or treatment.

Important information: Calcipotriene and Betamethasone Dipropionate Ointment is for use on the skin only (topical use only). Do not use Calcipotriene and Betamethasone Dipropionate Ointment on the face, under arms or on groin area. Do not swallow Calcipotriene and Betamethasone Dipropionate Ointment. Another product, Calcipotriene and Betamethasone Dipropionate Topical Suspension contains the same medicine that is in Calcipotriene and Betamethasone Dipropionate Ointment and is used to treat plaque psoriasis on the scalp. If you use both medicines to treat your plaque psoriasis, be sure to follow your doctor's directions carefully so that you do not use too much of one or both of these medications.

What is Calcipotriene and Betamethasone Dipropionate Ointment?

Calcipotriene and Betamethasone Dipropionate Ointment is a prescription medicine that is for use on the skin only (a topical medicine). Calcipotriene and Betamethasone Dipropionate Ointment is used to treat plaque psoriasis in patients 12 years of age and older.

Calcipotriene and Betamethasone Dipropionate Ointment has not been studied in patients under the age of 12 years.

Who should not use Calcipotriene and Betamethasone Dipropionate Ointment?

Do not use Calcipotriene and Betamethasone Dipropionate Ointment if you:

- have thin skin (atrophy) at the site to be treated
- are allergic to anything in Calcipotriene and Betamethasone Dipropionate Ointment. See the end of this leaflet for a complete list of ingredients.

What should I tell my doctor before using Calcipotriene and Betamethasone Dipropionate Ointment?

Tell your doctor about all of your health conditions, including if you:

- have a skin infection. Your skin infection should be treated before starting Calcipotriene and Betamethasone Dipropionate Ointment.
- have a calcium metabolism disorder
- have one of the following types of psoriasis:
  - erythrodermic psoriasis
  - exfoliative psoriasis
  - pustular psoriasis
- are getting phototherapy treatments (light therapy) for your psoriasis
- are pregnant or planning to become pregnant. It is not known if Calcipotriene and Betamethasone Dipropionate Ointment can harm your unborn baby. You and your doctor will have to decide if Calcipotriene and Betamethasone Dipropionate Ointment is right for you while pregnant.
- are breastfeeding or plan to breastfeed. It is not known if Calcipotriene and Betamethasone Dipropionate Ointment passes into your milk and if it can harm your baby. If you use Calcipotriene and Betamethasone Dipropionate Ointment while breastfeeding, use Calcipotriene and Betamethasone Dipropionate Ointment on the smallest area of skin and for the shortest time needed. If you use Calcipotriene and Betamethasone Dipropionate Ointment, do not apply Calcipotriene and Betamethasone Dipropionate Ointment to your nipple or areola to avoid getting Calcipotriene and Betamethasone Dipropionate Ointment into your baby's mouth.

Tell your doctor about all the medicines you take, including prescription, and nonprescription medicines, vitamins and herbal supplements.

Calcipotriene and Betamethasone Dipropionate Ointment and some other medicines can interact with each other. Especially tell your doctor if you use:

- other corticosteroid medicines
- other medicines for your psoriasis

How should I use Calcipotriene and Betamethasone Dipropionate Ointment?

- Use Calcipotriene and Betamethasone Dipropionate Ointment exactly as prescribed by your doctor.
- If you are 18 years of age or older, you should not use more than 100 grams of Calcipotriene and Betamethasone Dipropionate Ointment in 1 week.
- If you are 12 to 17 years of age, you should not use more than 60 grams of Calcipotriene and Betamethasone Dipropionate Ointment in 1 week.
- Apply Calcipotriene and Betamethasone Dipropionate Ointment once a day to the areas of your skin affected by psoriasis. Gently rub Calcipotriene and Betamethasone Dipropionate Ointment into your affected skin areas.
- Only use Calcipotriene and Betamethasone Dipropionate Ointment as directed by your doctor. Calcipotriene and Betamethasone Dipropionate Ointment is recommended for up to 4 weeks of treatment. Do not use Calcipotriene and Betamethasone Dipropionate Ointment for more than 4 weeks unless prescribed by your doctor.
- Do not use Calcipotriene and Betamethasone Dipropionate Ointment on the face, under arms or on groin area. If you accidentally get Calcipotriene and Betamethasone Dipropionate Ointment on the face or in the eyes wash the area with water right away.
- If you forget to use Calcipotriene and Betamethasone Dipropionate Ointment, use it as soon as you remember. Then go on as before.
- Wash your hands well after applying Calcipotriene and Betamethasone Dipropionate Ointment.
- If you are breastfeeding, do not use Calcipotriene and Betamethasone Dipropionate Ointment on the breast while nursing.

Using Calcipotriene and Betamethasone Dipropionate Ointment:

Do not bandage or tightly cover the treated skin area.

Remove the cap and check that the aluminum seal covers the tube before the first use. To break the seal, turn the cap over and punch through the seal.

What should I avoid while using Calcipotriene and Betamethasone Dipropionate Ointment?

Avoid spending a long time in the sunlight. Avoid tanning booths and sunlamps. Use sunscreen if you have to be in the sunlight. Talk to your doctor if you get a sunburn.

What are the possible side effects of Calcipotriene and Betamethasone Dipropionate Ointment?

The most common side effects are:

- itching
- rash

Other less common side effects with Calcipotriene and Betamethasone Dipropionate Ointment include:

- redness of the skin
- skin irritation
- skin burning
- inflamed hair pores (folliculitis)
- change of skin color (at the site of application)
- rash with pus-filled papules
- thinning of the skin (atrophy)
- swollen fine blood vessels (this makes your skin appear red at the site of application)

Calcipotriene and Betamethasone Dipropionate Ointment may cause serious side effects. Serious side effects are more likely to happen if you use too much Calcipotriene and Betamethasone Dipropionate Ointment, use it for too long, or use it with other topical medicines that contain corticosteroids, calcipotriene, or certain other ingredients. Check with your doctor before using other topical medicines. Calcipotriene and Betamethasone Dipropionate Ointment can pass through your skin. Serious side effects may include:

- too much calcium in your blood or urine
- adrenal gland problems

Your doctor may do special blood and urine tests to check your calcium levels and adrenal gland function while you are using Calcipotriene and Betamethasone Dipropionate Ointment.
Call your doctor about any side effect that bothers you or that does not go away.

These are not all of the side effects with Calcipotriene and Betamethasone Dipropionate Ointment. Ask your doctor or pharmacist for more information.

Vision problems. Calcipotriene and Betamethasone Dipropionate Ointment may increase your chance of developing cataract(s) and glaucoma. Tell your healthcare provider if you develop blurred vision or other vision problems during treatment with Calcipotriene and Betamethasone Dipropionate Ointment.

How should I store Calcipotriene and Betamethasone Dipropionate Ointment?

- Store Calcipotriene and Betamethasone Dipropionate Ointment at room temperature, 68°F - 77°F (20°C - 25°C); Make sure the cap on the tube is tightly closed.
- Calcipotriene and Betamethasone Dipropionate Ointment has an expiration date (exp.) marked on the tube. Do not use the ointment after this date.
- Keep Calcipotriene and Betamethasone Dipropionate Ointment and all medicines out of the reach of children and pets.

General information about Calcipotriene and Betamethasone Dipropionate Ointment

Medicines are sometimes prescribed for conditions that are not mentioned in patient information leaflets. Do not use Calcipotriene and Betamethasone Dipropionate Ointment for a condition for which it was not prescribed. Do not give Calcipotriene and Betamethasone Dipropionate Ointment to other people, even if they have the same symptoms you have. It may harm them.

This leaflet summarizes the most important information about Calcipotriene and Betamethasone Dipropionate Ointment. If you would like more information, talk with your doctor. You can ask your doctor or pharmacist for information about Calcipotriene and Betamethasone Dipropionate Ointment that is written for health professionals.

What are the ingredients in Calcipotriene and Betamethasone Dipropionate Ointment?

Active ingredients: calcipotriene hydrate, betamethasone dipropionate.
Inactive ingredients: butylhydroxytoluene, mineral oil, polyoxypropylene stearyl ether, all-rac-alpha-tocopherol, white petrolatum.

Manufactured by:
LEO Laboratories Ltd. (LEO Pharma)
Dublin 12, Ireland

Distributed by:
Prasco Laboratories
Mason, OH 45040 USA

Revised: 03/2020

PRINCIPAL DISPLAY PANEL - 60 g Tube Carton

NDC 66993-938-61
Rx only

PRASCO

Calcipotriene 0.005% and
Betamethasone Dipropionate 0.064%
Ointment

For Topical Use Only
Net Wt. 60 g

PRINCIPAL DISPLAY PANEL - 100 g Tube Carton

NDC 66993-938-65
Rx only

PRASCO

Calcipotriene 0.005% and
Betamethasone Dipropionate 0.064%
Ointment

For Topical Use Only
Net Wt. 100 g